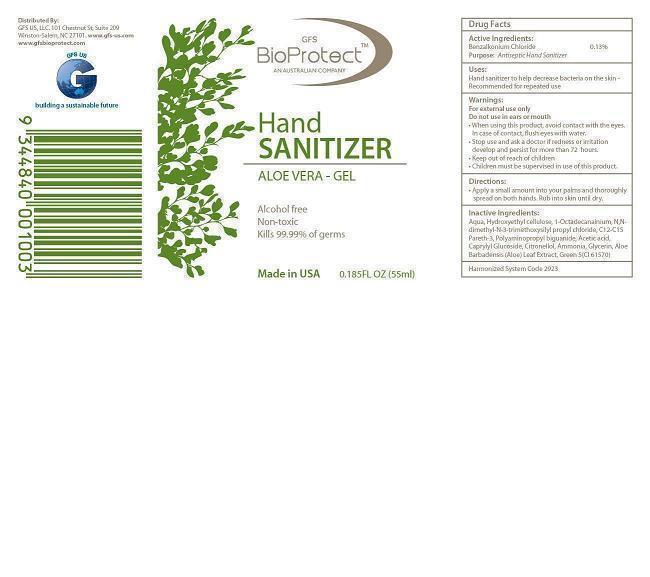 DRUG LABEL: GFS BioProtect Hand Sanitizer Aloe Vera
NDC: 76426-012 | Form: GEL
Manufacturer: GFS US LLC
Category: otc | Type: HUMAN OTC DRUG LABEL
Date: 20130403

ACTIVE INGREDIENTS: BENZALKONIUM CHLORIDE 0.0013 g/1 g
INACTIVE INGREDIENTS: Water; HYDROXYETHYL CELLULOSE (4000 MPA.S AT 1%); DIMETHYLOCTADECYL(3-(TRIMETHOXYSILYL)PROPYL)AMMONIUM CHLORIDE; C12-15 PARETH-12; POLYAMINOPROPYL BIGUANIDE; Acetic Acid; CAPRYLYL GLUCOSIDE; .BETA.-CITRONELLOL, (+/-)-; AMMONIA; GLYCERIN; ALOE VERA LEAF; D&C Green No. 5

DRUG FACTS

DESCRIPTION

BioProtect Hand Sanitizer contains 0.13% antiseptic agent Benzalkonium Chloride formulated with Water,Hydroxyethyl Cellulose, Alkyl Polyglucoside, C12-C15 Pareth-3, 1-Ocatadecanaminium, N-N-dimethyl-N-[3-(trimethoxysilyl)propyl]-,chloride, Polyhexamethylene
Biguanide, Acetic Acid, Citronellol, Ammonia, Glycerin, Aloe Barbadensis (Aloe) Leaf Extract, and D and C Green No.5. It is alcohol-free, non-toxic and kills 99.99% of germs.

ACTIVE INGREDIENT

- Benzalkonium Chloride 0.13%.............................................Antiseptic

PURPOSE

- Antiseptic

INDICATIONS AND USAGE

- Hand sanitizer to help decrease bacteria on skin
- Recommended for repeated use

WARNINGS

- For external use only
- Do not use in ears or mouth

- Keep out of reach on children
- Children must be supervised in use of this product

DOSAGE AND ADMINISTRATION

- Apply a small amount into your palm and throughly spread on both hands
- Rub into skin until dry

GENERAL PRECAUTIONS

- Review MSDS before handling the product

- When using this product do not use in ears or mouth
- Avoid contact with eyes
- In case of eye contact, rinse eyes thoroughly with water

- Stop use and ask a doctor if skin irritation or redness develops and persists for more than 72 hours

INACTIVE INGREDIENT

- Water; Hydroxyethyl Cellulose; Alkyl Polyglucoside; C12-C15 Pareth-3; 1-Ocatadecanaminium,N-N-dimethyl-N-[3-(trimethoxysilyl)propyl]-,chloride; Polyhexamethylene Biguanide; Acetic Acid; Citronellol; Ammonia; Glycerin; AloeBarbadensis (Aloe) Leaf Extract; D and C Green No.5

Label